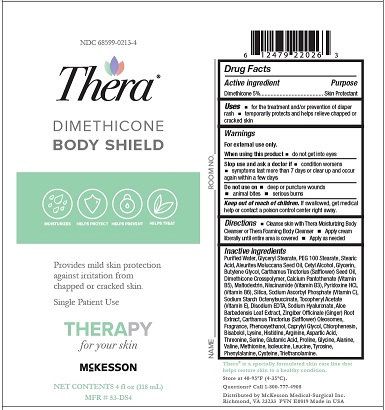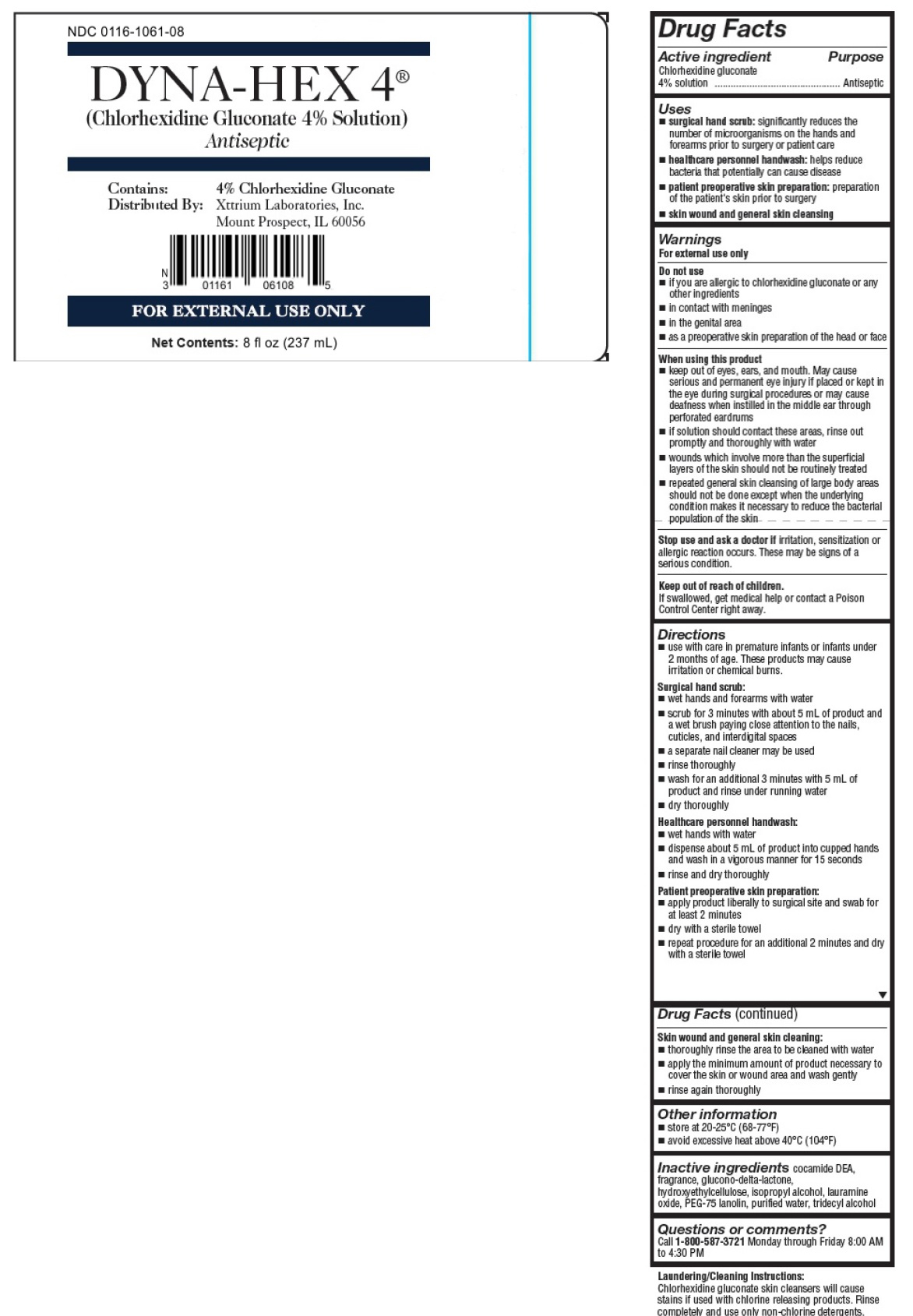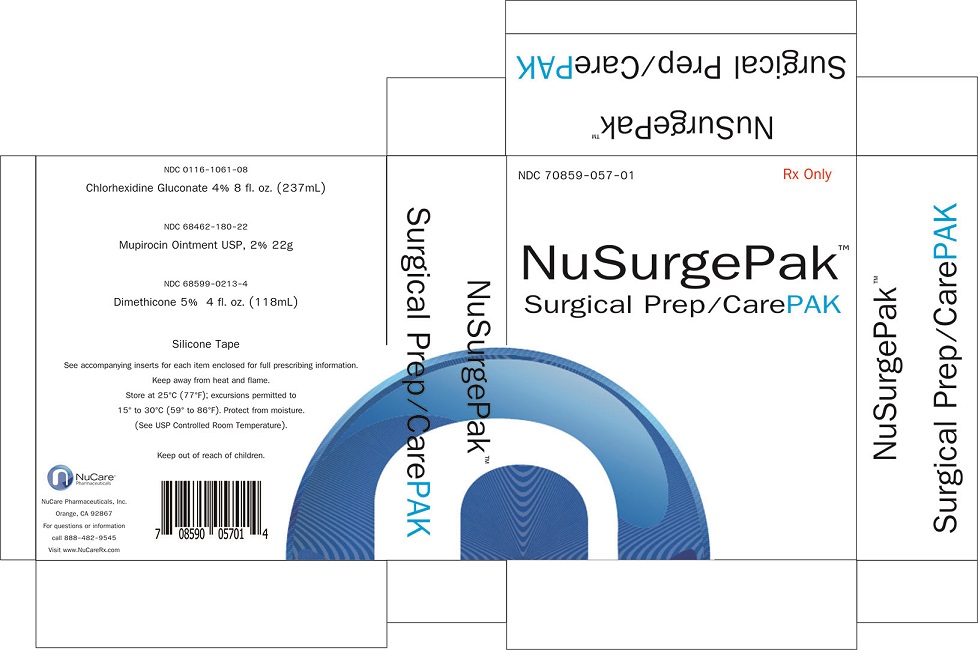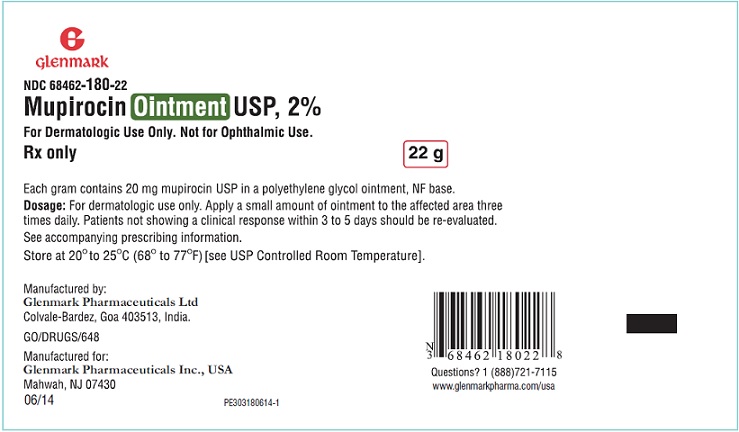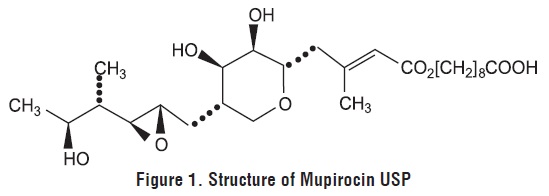 DRUG LABEL: NuSurgePak Surgical Prep/CarePak
NDC: 70859-057 | Form: KIT | Route: TOPICAL
Manufacturer: Nucare Pharmaceuticals Inc
Category: prescription | Type: HUMAN PRESCRIPTION DRUG LABEL
Date: 20200622

ACTIVE INGREDIENTS: CHLORHEXIDINE GLUCONATE 4 g/100 mL; MUPIROCIN 20 mg/1 g; DIMETHICONE 50 ug/1 mg
INACTIVE INGREDIENTS: HYDROXYETHYL CELLULOSE (2000 CPS AT 1%); ISOPROPYL ALCOHOL; LAURAMINE OXIDE; WATER; TRIDECYL ALCOHOL; GLUCONOLACTONE; COCO DIETHANOLAMIDE; PEG-75 LANOLIN; POLYETHYLENE GLYCOL 400; POLYETHYLENE GLYCOL 3350; ISOLEUCINE; TROLAMINE; OCTENYLSUCCINIC ACID; GLUTAMIC ACID; SERINE; KUKUI NUT OIL; ALOE VERA LEAF; ALANINE; GLYCINE; STEARIC ACID; LYSINE; SILICON DIOXIDE; PHENOXYETHANOL; NIACINAMIDE; CHLORPHENESIN; LEVOMENOL; GLYCERYL MONOSTEARATE; CALCIUM PANTOTHENATE; ARGININE; PYRIDOXINE HYDROCHLORIDE; DIMETHICONE CROSSPOLYMER (450000 MPA.S AT 12% IN CYCLOPENTASILOXANE); WATER; ASPARTIC ACID; GLYCERIN; HYALURONATE SODIUM; VALINE; GINGER; HISTIDINE; PROLINE; LEUCINE; CYSTEINE; METHIONINE; SAFFLOWER OIL; BUTYLENE GLYCOL; PHENYLALANINE; .ALPHA.-TOCOPHEROL ACETATE; CARTHAMUS TINCTORIUS (SAFFLOWER) OLEOSOMES; PEG-100 STEARATE; CETYL ALCOHOL; MALTODEXTRIN; SODIUM ASCORBYL PHOSPHATE; EDETATE DISODIUM ANHYDROUS; TYROSINE; THREONINE; CAPRYLYL GLYCOL

1 INDICATIONS AND USAGE

Mupirocin ointment is indicated for the topical treatment of impetigo due to susceptible isolates of Staphylococcus aureus (S. aureus) and Streptococcus pyogenes (S. pyogenes).

2 DOSAGE AND ADMINISTRATION

- For Topical Use Only.
- Apply a small amount of mupirocin ointment, with a cotton swab or gauze pad, to the affected area 3 times daily for up to 10 days.
- Cover the treated area with gauze dressing if desired.
- Re-evaluate patients not showing a clinical response within 3 to 5 days.
- Mupirocin ointment is not for intranasal, ophthalmic, or other mucosal use [see Warnings and Precautions (5.2, 5.6)].
- Do not apply mupirocin ointment concurrently with any other lotions, creams or ointments [see Clinical Pharmacology (12.3)].

3 DOSAGE FORMS AND STRENGTHS

- Ointment: Each gram contains 20 mg mupirocin USP in a water-miscible ointment base supplied in 22-gram tubes. (3)

4 CONTRAINDICATIONS

- Known hypersensitivity to mupirocin or any of the excipients of mupirocin ointment. (4)

Mupirocin ointment is contraindicated in patients with known hypersensitivity to mupirocin or any of the excipients of mupirocin ointment.

5 WARNINGS AND PRECAUTIONS

- Severe Allergic Reactions: Anaphylaxis, urticaria, angioedema, and generalized rash have been reported in patients treated with formulations of mupirocin, including mupirocin ointment. (5.1)
- Eye Irritation: Avoid contact with eyes. (5.2)
- Local Irritation: Discontinue in the event of sensitization or severe local irritation. (5.3)
- Clostridium difficile-Associated Diarrhea (CDAD): If diarrhea occurs, evaluate patients for CDAD. (5.4)
- Potential for Microbial Overgrowth: Prolonged use may result in overgrowth of nonsusceptible microorganisms, including fungi. (5.5)
- Risk Associated with Mucosal Use: Mupirocin ointment is not formulated for use on mucosal surfaces. A separate formulation, BACTROBAN nasal ointment, is available for intranasal use. (5.6)
- Risk of Polyethylene Glycol Absorption: Mupirocin ointment should not be used where absorption of large quantities of polyethylene glycol is possible, especially if there is evidence of moderate or severe renal impairment. (5.7)
- Risk Associated with Use at Intravenous Sites: Mupirocin ointment should not be used with intravenous cannulae or at central intravenous sites because of the potential to promote fungal infections and antimicrobial resistance. (5.8)

5.1 Severe Allergic Reactions

Systemic allergic reactions, including anaphylaxis, urticaria, angioedema, and generalized rash, have been reported in patients treated with formulations of mupirocin, including mupirocin ointment [see Adverse Reactions (6.2)].

5.2 Eye Irritation

Avoid contact with the eyes. In case of accidental contact, rinse well with water.

5.3 Local Irritation

In the event of a sensitization or severe local irritation from mupirocin ointment, usage should be discontinued, and appropriate alternative therapy for the infection instituted.

5.4 Clostridium difficile-Associated Diarrhea

Clostridium difficile-associated diarrhea (CDAD) has been reported with use of nearly all antibacterial agents and may range in severity from mild diarrhea to fatal colitis. Treatment with antibacterial agents alters the normal flora of the colon leading to overgrowth of C. difficile.

C. difficile produces toxins A and B which contribute to the development of CDAD. Hypertoxin-producing strains of C. difficile cause increased morbidity and mortality, as these infections can be refractory to antimicrobial therapy and may require colectomy. CDAD must be considered in all patients who present with diarrhea following antibacterial drug use. Careful medical history is necessary since CDAD has been reported to occur over 2 months after the administration of antibacterial agents.

If CDAD is suspected or confirmed, ongoing antibacterial drug use not directed against C. difficile may need to be discontinued. Appropriate fluid and electrolyte management, protein supplementation, antibacterial treatment of C. difficile, and surgical evaluation should be instituted as clinically indicated.

5.5 Potential for Microbial Overgrowth

As with other antibacterial products, prolonged use of mupirocin ointment may result in overgrowth of nonsusceptible microorganisms, including fungi [see Dosage and Administration (2)].

5.6 Risk Associated with Mucosal Use

Mupirocin ointment is not formulated for use on mucosal surfaces. Intranasal use has been associated with isolated reports of stinging and drying. A separate formulation,†Bactroban (mupirocin calcium) nasal ointment, is available for intranasal use.

5.7 Risk of Polyethylene Glycol Absorption

Polyethylene glycol can be absorbed from open wounds and damaged skin and is excreted by the kidneys. In common with other polyethylene glycol-based ointments, mupirocin ointment should not be used in conditions where absorption of large quantities of polyethylene glycol is possible, especially if there is evidence of moderate or severe renal impairment.

5.8 Risk Associated with Use at Intravenous Sites

Mupirocin ointment should not be used with intravenous cannulae or at central intravenous sites because of the potential to promote fungal infections and antimicrobial resistance.

6 ADVERSE REACTIONS

- The most frequent adverse reactions (at least 1%) were burning, stinging or pain, and itching. (6.1)

To report SUSPECTED ADVERSE REACTIONS, contact Glenmark Pharmaceuticals Inc., USA at 1-888-721-7115 or FDA at 1-800-FDA-1088 or www.fda.gov/medwatch.

The following adverse reactions are discussed in more detail in other sections of the labeling:

- Severe Allergic Reactions [see Warnings and Precautions (5.1)]
- Eye Irritation [see Warnings and Precautions (5.2)]
- Local Irritation [see Warnings and Precautions (5.3)]
- Clostridium difficile-Associated Diarrhea [see Warnings and Precautions (5.4)]

6.1 Clinical Trials Experience

Because clinical trials are conducted under widely varying conditions, adverse reaction rates observed in the clinical trials of a drug cannot be directly compared with rates in the clinical trials of another drug and may not reflect the rates observed in practice.

The following local adverse reactions were reported by at least 1% of subjects in connection with the use of mupirocin ointment in clinical trials: burning, stinging, or pain in 1.5% of subjects; itching in 1% of subjects. Rash, nausea, erythema, dry skin, tenderness, swelling, contact dermatitis, and increased exudate were reported in less than 1% of subjects.

6.2 Postmarketing Experience

In addition to adverse reactions reported from clinical trials, the following reactions have been identified during postmarketing use of mupirocin ointment. Because they are reported voluntarily from a population of unknown size, estimates of frequency cannot be made. These reactions have been chosen for inclusion due to a combination of their seriousness, frequency of reporting, or potential causal relationship to mupirocin ointment.

Immune System Disorders

Systemic allergic reactions, including anaphylaxis, urticaria, angioedema, and generalized rash [see Warnings and Precautions (5.1)].

8 USE IN SPECIFIC POPULATIONS

Click here to enter Use in Specific Populations

8.1 Pregnancy

Risk Summary

There are insufficient human data to establish whether there is a drug-associated risk with mupirocin ointment in pregnant women. Systemic absorption of mupirocin through intact human skin is minimal following topical administration of mupirocin ointment [see Clinical Pharmacology (12.3)] . No developmental toxicity was observed in rats or rabbits treated with mupirocin subcutaneously during organogenesis at doses of 160 or 40 mg per kg per day, respectively (22 and 11 times the human topical dose based on calculations of dose divided by the entire body surface area).

The estimated background risk of major birth defects and miscarriages for the indicated population is unknown. The estimated background risk in the U.S. general population of major birth defects is 2% to 4% and of miscarriage is 15% to 20% of clinically recognized pregnancies.

Data

Animal Data: Developmental toxicity studies have been performed with mupirocin administered subcutaneously to rats and rabbits at doses up to 160 mg per kg per day during organogenesis. This dose is 22 and 43 times, respectively, the human topical dose (approximately 60 mg mupirocin per day) based on calculations of dose divided by the entire body surface area. Maternal toxicity was observed (body weight loss/decreased body weight gain and reduced feeding) in both species with no evidence of developmental toxicity in rats. In rabbits, excessive maternal toxicity at the high dose precluded the evaluation of fetal outcomes. There was no developmental toxicity in rabbits at 40 mg per kg per day, 11 times the human topical dose based on calculations of dose divided by the entire body surface area.

Mupirocin administered subcutaneously to rats in a pre-and postnatal development study (dosed during late gestation through lactation) was associated with reduced offspring viability in the early postnatal period at a dose of 106.7 mg per kg, in the presence of injection site irritation and/or subcutaneous hemorrhaging. This dose is 14 times the human topical dose based on calculations of dose divided by the entire body surface area. The no-observed adverse effect level in this study was 44.2 mg per kg per day, which is 6 times the human topical dose.

8.2 Lactation

Risk Summary

It is not known whether mupirocin is present in human milk, has effects on the breastfed child, or has effects on milk production. However, breastfeeding is not expected to result in exposure of the child to the drug due to the minimal systemic absorption of mupirocin in humans following topical administration of mupirocin ointment [see Clinical Pharmacology (12.3)] . The developmental and health benefits of breastfeeding should be considered along with the mother’s clinical need for mupirocin ointment and any potential adverse effects on the breastfed child from mupirocin ointment or from the underlying maternal condition.

Clinical Considerations

To minimize oral exposure of the drug to children, a breast and/or nipple being treated with mupirocin ointment should be thoroughly washed prior to breastfeeding.

8.4 Pediatric Use

The safety and effectiveness of mupirocin ointment have been established in the age range of 2 months to 16 years. Use of mupirocin ointment in these age-groups is supported by evidence from adequate and well-controlled trials of mupirocin ointment in impetigo in pediatric subjects studied as a part of the pivotal clinical trials [see Clinical Studies (14)].

11 DESCRIPTION

Mupirocin ointment USP 2% contains the RNA synthetase inhibitor antibacterial, mupirocin USP. The chemical name is (E)-(2 S,3 R,4 R,5 S)-5-[(2 S,3 S,4 S,5 S)-2,3-epoxy-5-hydroxy-4-methylhexyl]tetrahydro-3,4dihydroxy-ß-methyl-2 H-pyran-2-crotonic acid, ester with 9-hydroxynonanoic acid. The molecular formula of mupirocin USP is C26H44O9, and the molecular weight is 500.6. The chemical structure is:

Each gram of mupirocin ointment USP 2% contains 20 mg mupirocin USP in a water-miscible ointment base (polyethylene glycol ointment, N.F.) consisting of polyethylene glycol 400 and polyethylene glycol 3350.

12 CLINICAL PHARMACOLOGY

Click here to enter Clinical Pharmacology

12.1 Mechanism of Action

Mupirocin is an RNA synthetase inhibitor antibacterial [see Microbiology (12.4)].

12.3 Pharmacokinetics

Absorption

Application of^14C-labeled mupirocin ointment to the lower arm of normal male subjects followed by occlusion for 24 hours showed no measurable systemic absorption (less than 1.1 nanogram mupirocin per milliliter of whole blood). Measurable radioactivity was present in the stratum corneum of these subjects 72 hours after application.

The effect of the concurrent application of mupirocin ointment with other drug products has not been studied [see Dosage and Administration (2)].

Elimination

In a trial conducted in 7 healthy adult male subjects, the elimination half-life after intravenous administration of mupirocin was 20 to 40 minutes for mupirocin and 30 to 80 minutes for monic acid.

Metabolism: Following intravenous or oral administration, mupirocin is rapidly metabolized. The principal metabolite, monic acid, demonstrates no antibacterial activity.

Excretion: Monic acid is predominantly eliminated by renal excretion.

12.4 Microbiology

Mupirocin is an RNA synthetase inhibitor antibacterial produced by fermentation using the organism Pseudomonas fluorescens.

Mechanism of Action

Mupirocin inhibits bacterial protein synthesis by reversibly and specifically binding to bacterial isoleucyltransfer RNA (tRNA) synthetase.

Mupirocin is bactericidal at concentrations achieved by topical administration. Mupirocin is highly protein bound (greater than 97%) and the effect of wound secretions on the minimum inhibitory concentrations (MICs) of mupirocin has not been determined.

Mechanism of Resistance

When mupirocin resistance occurs, it results from the production of a modified isoleucyl-tRNA synthetase, or the acquisition of, by genetic transfer, a plasmid mediating a new isoleucyl-tRNA synthetase. High-level plasmid-mediated resistance (MIC =512 mcg/mL) has been reported in increasing numbers of isolates of S. aureus and with higher frequency in coagulase-negative staphylococci. Mupirocin resistance occurs with greater frequency in methicillin-resistant than methicillin-susceptible staphylococci.

Cross Resistance

Due to its mode of action, mupirocin does not demonstrate cross resistance with other classes of antimicrobial agents.

Antimicrobial Activity

Mupirocin has been shown to be active against susceptible isolates of S. aureus and S. pyogenes, both in vitro and in clinical trials [see Indications and Usage (1)]. The following in vitro data are available, but their clinical significance is unknown. Mupirocin is active against most isolates of Staphylococcus epidermidis.

Susceptibility Testing

High-level mupirocin resistance (=512 mcg/mL) may be determined using standard disk diffusion or broth microdilution tests.^1,2 Because of the occurrence of mupirocin resistance in methicillin-resistant S. aureus (MRSA), it is appropriate to test MRSA populations for mupirocin susceptibility prior to the use of mupirocin using a standardized method.^3,4,5

13 NONCLINICAL TOXICOLOGY

13.1 Carcinogenesis, Mutagenesis, Impairment of Fertility

Long-term studies in animals to evaluate carcinogenic potential of mupirocin have not been conducted.

Results of the following studies performed with mupirocin calcium or mupirocin sodium in vitro and in vivo did not indicate a potential for genotoxicity: rat primary hepatocyte unscheduled DNA synthesis, sediment analysis for DNA strand breaks, Salmonella reversion test (Ames), Escherichia coli mutation assay, metaphase analysis of human lymphocytes, mouse lymphoma assay, and bone marrow micronuclei assay in mice.

In a fertility/reproductive performance study (with dosing through lactation), mupirocin administered subcutaneously to male and female rats at doses up to 100 mg per kg per day which is 14 times the human topical dose (approximately 60 mg mupirocin per day) based on calculations of dose divided by the entire body surface area, did not result in impaired fertility or impaired reproductive performance attributable to mupirocin.

14 CLINICAL STUDIES

The efficacy of topical mupirocin ointment in impetigo was tested in 2 trials. In the first, subjects with impetigo were randomized to receive either mupirocin ointment or vehicle placebo 3 times daily for 8 to 12 days. Clinical efficacy rates at end of therapy in the evaluable populations (adults and pediatric subjects included) were 71% for mupirocin ointment (n = 49) and 35% for vehicle placebo (n = 51). Pathogen eradication rates in the evaluable populations were 94% for mupirocin ointment and 62% for vehicle placebo.

In the second trial, subjects with impetigo were randomized to receive either mupirocin ointment 3 times daily or 30 to 40 mg per kg oral erythromycin ethylsuccinate per day (this was an unblinded trial) for 8 days. There was a follow-up visit 1 week after treatment ended. Clinical efficacy rates at the follow-up visit in the evaluable populations (adults and pediatric subjects included) were 93% for mupirocin ointment (n = 29) and 78.5% for erythromycin (n = 28). Pathogen eradication rates in the evaluable populations were 100% for both test groups.

Pediatrics

There were 91 pediatric subjects aged 2 months to 15 years in the first trial described above. Clinical efficacy rates at end of therapy in the evaluable populations were 78% for mupirocin ointment (n = 42) and 36% for vehicle placebo (n = 49). In the second trial described above, all subjects were pediatric except 2 adults in the group receiving mupirocin ointment. The age range of the pediatric subjects was 7 months to 13 years. The clinical efficacy rate for mupirocin ointment (n = 27) was 96%, and for erythromycin it was unchanged (78.5%).

15 REFERENCES

1. Clinical and Laboratory Standards Institute (CLSI). Performance Standards for Antimicrobial Susceptibility Testing; Twenty-fifth Informational Supplement. CLSI document M100-S25. Clinical and Laboratory Standards Institute, 950 West Valley Rd., Suite 2500, Wayne, PA 19087, USA, 2015.
2. Patel J, Gorwitz RJ, et al. Mupirocin Resistance. Clinical Infectious Diseases. 2009; 49(6): 935-41.
3. Clinical and Laboratory Standards Institute (CLSI). Methods for Dilution Antimicrobial Susceptibility Tests for Bacteria that Grow Aerobically; Approved Standard – Tenth Edition. CLSI document M07-A10. Clinical and Laboratory Standards Institute, 950 West Valley Road, Suite 2500, Wayne, Pennsylvania 19087, USA, 2015.
4. Clinical and Laboratory Standards Institute (CLSI). Performance Standards for Antimicrobial Disk Diffusion Susceptibility Tests; Approved Standard – Twelfth Edition. CLSI document M02-A12. Clinical and Laboratory Standards Institute, 950 West Valley Road, Suite 2500, Wayne, Pennsylvania 19087, USA, 2015.
5. Finlay JE, Miller LA, Poupard JA. Interpretive criteria for testing susceptibility of staphylococci to mupirocin. Antimicrob Agents Chemother 1997;41(5):1137-1139.

16 HOW SUPPLIED/STORAGE AND HANDLING

Mupirocin ointment USP 2% is supplied in 22-gram tubes.

Each gram of mupirocin ointment USP contains 20 mg mupirocin USP in a water-miscible ointment base.

NDC 68462-180-22 22-gram tube (1 tube per carton)

Store at 20° to 25°C (68° to 77°F) [see USP Controlled Room Temperature].

17 PATIENT COUNSELING INFORMATION

Advise the patient to read the FDA-approved patient labeling (Patient Information).

Advise the patient to administer mupirocin ointment as follows:

- Use mupirocin ointment only as directed by the healthcare provider. It is for external use only. Avoid contact of mupirocin ointment with the eyes. If mupirocin ointment gets in the eyes, rinse thoroughly with water.
- Do not use mupirocin ointment in the nose.
- Wash your hands before and after applying mupirocin ointment.
- Use a gauze pad or cotton swab to apply a small amount of mupirocin ointment to the affected area. The treated area may be covered by gauze dressing if desired.
- Report to the healthcare provider any signs of local adverse reactions. Mupirocin ointment should be stopped and the healthcare provider contacted if irritation, severe itching, or rash occurs.
- Report to the healthcare provider or go to the nearest emergency room if severe allergic reactions, such as swelling of the lips, face, or tongue, or wheezing occur [see Warnings and Precautions (5.1)].
- If impetigo has not improved in 3 to 5 days, contact the healthcare provider.

†Bactroban is a registered trademark of the GSK group of companies.

Manufactured by:

Glenmark Pharmaceuticals Ltd.
Colvale-Bardez, Goa 403 513, India

Manufactured for:

Glenmark Pharmaceuticals Inc., USA
Mahwah, NJ 07430

Questions? 1 (888)721-7115
www.glenmarkpharma.com/usa

December 2015

Patient Information

Mupirocin (mue-PIR-oh-sin)
Ointment USP

What is mupirocin ointment?

Mupirocin ointment is a prescription medicine used on the skin (topical use) to treat a skin infection called impetigo that is caused by bacteria called Staphylococcus aureus and Streptococcus pyogenes. It is not known if mupirocin ointment is safe and effective in children under 2 months of age.

Who should not use mupirocin ointment?

Do not use mupirocin ointment if:

- you are allergic to mupirocin or any of the ingredients in mupirocin ointment. See the end of this Patient Information leaflet for a complete list of the ingredients in mupirocin ointment.

What should I tell my healthcare provider before using mupirocin ointment?

Before using mupirocin ointment, tell your healthcare provider about all of your medical conditions including if you:

- have kidney problems
- are pregnant or plan to become pregnant. It is not known if mupirocin ointment will harm your unborn baby.
- are breastfeeding or plan to breastfeed. It is not known if mupirocin ointment passes into your breast milk. You and your healthcare provider should decide if you can use mupirocin ointment while breastfeeding.

Tell your healthcare provider about all of the medicines you take, including prescription and over-the-counter medicines, vitamins, and herbal supplements. Do not mix mupirocin ointment with other lotions, creams, or ointments.

How should I use mupirocin ointment?

- Mupirocin ointment is for use on the skin (topical). Do not get mupirocin ointment in your eyes, nose, mouth, or vagina (mucosal surfaces).
- Use mupirocin ointment exactly as your healthcare provider tells you to use it.
- Apply a small amount of mupirocin ointment, with a cotton swab or gauze pad, to the affected area 3 times each day.
- It is important that you take the full course of mupirocin ointment. Do not stop early because your symptoms may disappear before the infection is fully cleared.
- Wash your hands before and after applying mupirocin ointment.
- After applying mupirocin ointment, you may cover the treated area with a clean gauze pad, unless your healthcare provider has told you to leave it uncovered.
- Talk to your healthcare provider if your skin does not improve after 3 to 5 days of treatment with mupirocin ointment.

What are the possible side effects of mupirocin ointment?

Mupirocin ointment may cause serious side effects, including:

- severe allergic reactions. Stop using mupirocin ointment and call your healthcare provider or go to the nearest emergency room right away if you have any of the following signs or symptoms of a severe allergic reaction:
- hives
- trouble breathing or wheezing
- swelling of your face, lips, mouth, or tongue
- dizziness, fast heartbeat, or pounding in your chest
- a rash over your whole body
- eye irritation. Do not get mupirocin ointment in your eyes. If mupirocin ointment gets in your eyes, rinse your eyes well with water.
- irritation in the area mupirocin ointment is used. Stop using mupirocin ointment and call your healthcare provider if you develop an irritation, severe itching, or a rash while using mupirocin ointment.
- a type of diarrhea called clostridium difficile-associated diarrhea (CDAD). CDAD may happen in people who use or have used medicine to treat bacterial infections. The severity of CDAD can range from mild diarrhea to severe diarrhea that may cause death (fatal colitis). Call your healthcare provider or go to the nearest emergency room right away if you have diarrhea while using or after you stop using mupirocin ointment.
- risk of absorption of polyethylene glycol through the skin. Mupirocin ointment contains polyethylene glycol, which in large amounts can cause kidney damage. You should not apply mupirocin ointment to open skin wounds or damaged skin, especially if you have kidney problems.
- increased risk of infection at IV (intravenous) sites. Mupirocin ointment should not be used on skin that is near an IV (intravenous) site

The most common side effects of mupirocin ointment include:

- burning
- stinging or pain
- itching

These are not all the possible side effects of mupirocin ointment. Call your doctor for medical advice about side effects. You may report side effects to FDA at 1-800-FDA-1088.

How should I store mupirocin ointment?

- Store at 20° to 25°C (68° to 77°F).

Keep mupirocin ointment and all medicines out of the reach of children.

General information about the safe and effective use of mupirocin ointment

Medicines are sometimes prescribed for purposes other than those listed in a Patient Information leaflet. Do not use mupirocin ointment for a condition for which it was not prescribed. Do not give mupirocin ointment to other people, even if they have the same symptoms that you have. It may harm them. You can ask your pharmacist or healthcare provider for information about mupirocin ointment that is written for health professionals.

What are the ingredients in mupirocin ointment?

Active Ingredient: mupirocin USP

Inactive Ingredients: polyethylene glycol 400 and polyethylene glycol 3350

†Bactroban is a registered trademark of the GSK group of companies.

Manufactured by:

Glenmark Pharmaceuticals Ltd.
Colvale-Bardez, Goa 403 513, India

Manufactured for:

Glenmark Pharmaceuticals Inc., USA
Mahwah, NJ 07430

Questions? 1 (888)721-7115
www.glenmarkpharma.com/usa

December 2015

ACTIVE INGREDIENT

Chlorhexidine Gluconate

PURPOSE

Antiseptic

USES

- surgical hand scrub: significantly reduces the number of microorganisms on the hands and forearms prior to surgery or patient care
- healthcare personnel handwash: helps reduce bacteria that potentially can cause disease
- patient preoperative skin preparation: for the preparation of the patient's skin prior to surgeryskin wound and general skin cleansing
- skin wound and general skin cleansing

WARNINGS

For external use only.

Allergy alert:

This product may cause a severe allergic reaction. Symptoms may include:

- wheezing/difficulty breathing
- shock
- facial swelling
- hives
- rash

If an allergic reaction occurs, stop use and seek medical help right away.

DO NOT USE

- if you are allergic to chlorhexidine gluconate or any other ingredients
- in contact with meninges
- in the genital area
- as a preoperative skin preparation of the head or face

WHEN USING THIS PRODUCT

- keep out of eyes, ears, and mouth. May cause serious and permanent eye injury if placed or kept in the eye during surgical procedures or may cause deafness when instilled in the middle ear through perforated eardrums.
- if solution should contact these areas, rinse out promptly and thoroughly with water
- wounds which involve more than the superficial layers of the skin should not be routinely treated
- repeated general skin cleansing of large body areas should not be done except when advised by a health care provider

STOP USE AND ASK DOCTOR IF

if irritation, sensitization or allergic reaction occurs. These may be signs of a serious condition.

KEEP OUT OF REACH OF CHILDREN

if swallowed, get medical help or contact a Poison Control Center right away.

DIRECTION

- use with care in premature infants and infants under 2 months of age. These products may cause irritation or chemical burns.

Surgical hand scrub:

- wet hands and forearms with water
- scrub for 3 minutes with about 5 ml of product and a wet brush paying close attention to the nails, cuticles and interdigital spaces
- a separate nail cleaner may be used
- rinse thoroughly
- wash for an additional 3 minutes with 5 ml of product and rinse under running water
- dry thoroughly

Healthcare personnel handwash:

- wet hands with water
- dispense about 5 ml of product into cupped hands and wash in a vigorous manner for 15 seconds
- rinse and dry thoroughly

Patient preoperative skin preparation:

- apply product liberally to surgical site and swab for at least 2 minutes and dry with a sterile towel
- repeat procedure for an additional 2 minutes and dry with a sterile towel

Skin wound and general skin cleaning:

- thoroughly rinse the area to be cleaned with water
- apply the minimum amount of product necessary to cover the skin or wound area and wash gently
- rinse again thoroughly

OTHER INFORMATION

- store at 20-25ºC (68-77ºF)
- avoid excessive heat above 40ºC (104ºF)

INACTIVE INGREDIENTS

cocamide DEA, fragrance, glucono-delta-lactone, hydroxyethylcellulose, isopropyl alcohol, lauramine oxide, PEG-75 lanolin, purified water, tridecyl alcohol

QUESTIONS OR COMMENTS?

call 1-800-587-3721 Monday through Friday 8:00 AM to 4:30 PM CST

DIMETHICONE ,118mL(68599-0213-4)

Drug Facts

ACTIVE INGREDIENTS

Dimethicone 5.0%

PURPOSE

Skin Protectant

INDICATIONS & USAGE

Uses

For the treatment and / or prevention of diaper rash temporarily and helps relieve chapped or cracked skin

WARNINGS

For external use only.

- When using this product
- do not get into eyes

Do not use on

- deep or puncture wounds
- animal bites
- serious burns

STOP USE

Stop use and ask a doctor if

Condition worsens

symptoms last more than 7 days or clear up occur again within a few days

KEEP OUT OF REACH OF CHILDREN

If swallowed, get medical help or contact a Poison Control Center right away

DOSAGE & ADMINISTRATION

Directions

- Cleanse skin with Thera Moisturizing Body Cleanser or Thera Foaming Body Cleanser
- Apply cream liberally until entire area is covered
- Apply as needed

OTHER INFORMATION

Store at 40-95ºF (4-35ºC)

INACTIVE INGREDIENTS

Purified Water, Glyceryl Stearate, PEG 100 Stearate, Stearic Acid, Aleurites Moluccana Seed Oil,
Cetyl Alcohol, Glycerin, Butylene Glycol, Carthamus Tinctorius (Safflower) Seed Oil,
Dimethicone Crosspolymer, Calcium Pantothenate (Vitamin B5), Maltodextrin, Niacinamide (Vitamin B3),
Pyridoxine HCL (Vitamin B6), Silica, Sodium Ascorbyl Phosphate (Vitamin C), Sodium Starch Octenylsuccinate,
Tocopheryl Acetate (Vitamin E), Disodium EDTA, Sodium Hyaluronate, Aloe Barbadensis Leaf Extract,
Zingiber Officinale (Ginger) Root Extract, Carthamus Tinctorius (Safflower) Oleosomes, Fragrance,
Phenoxyethanol, Caprylyl Glycol, Chlorphenesin, Bisabolol, Lysine, Histidine, Arginine, Aspartic Acid,
Threonine, Serine, Glutamic Acid, Proline, Glycine, Alanine, Valine, Methionine, Isoleucine, Leucine,
Tyrosine, Phenylalanine, Cysteine, Triethanolamine

QUESTIONS

Call 1-800-777-4908

MUPIROCIN OINTMENT 68462-180-22

NDC 68462-180-22
Mupirocin Ointment USP, 2% - 22 g

CHLORHEXIDINE GLUCONATE 0116-1061-08

NDC 0116-1061-08

DYNA-HEX 4®

(Chlorhexidine Gluconate 4% Solution)

Antiseptic

Contains: 4% Chlorhexidine Gluconate

Distributed by: Xttrium Laboratories, Inc., Mount Prospect, IL 60056

FOR EXTERNAL USE ONLY

Net Contents: 4 fl oz (237 ml)